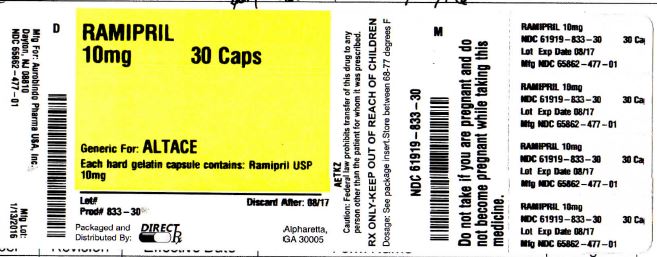 DRUG LABEL: RAMIPRIL
NDC: 61919-833 | Form: CAPSULE, GELATIN COATED
Manufacturer: DIRECT RX
Category: prescription | Type: HUMAN PRESCRIPTION DRUG LABEL
Date: 20160209

ACTIVE INGREDIENTS: RAMIPRIL 10 mg/1 1
INACTIVE INGREDIENTS: SILICON DIOXIDE; STARCH, CORN; GELATIN; SODIUM LAURYL SULFATE; FERROSOFERRIC OXIDE; SHELLAC; FD&C BLUE NO. 1; TITANIUM DIOXIDE

RAMIPRIL 10mg